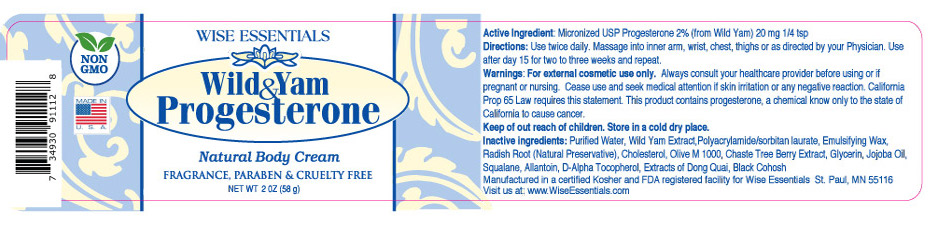 DRUG LABEL: Wild Yam and Progesterone
NDC: 87250-102 | Form: CREAM
Manufacturer: Wise Essentials LLC
Category: otc | Type: HUMAN OTC DRUG LABEL
Date: 20260123

ACTIVE INGREDIENTS: PROGESTERONE 20 mg/58 g
INACTIVE INGREDIENTS: GLYCERIN 30 mg/58 g; RADISH 20 mg/58 g; COCO-CAPRYLATE/CAPRATE 20 mg/58 g; SQUALANE 1 mg/58 g; CHOLESTEROL 20 mg/58 g; DIOSCOREA VILLOSA ROOT 80 mg/58 g; JOJOBA OIL 5 mg/58 g; SORBITAN OLIVATE 10 mg/58 g; CHASTE TREE 10 mg/58 g; ALLANTOIN 2 mg/58 g

Wild Yam and Progesterone

ACTIVE INGREDIENT

Micronized Progesterone USP, (Wild Yam) 2%

KEEP OUT OF REACH OF CHILDREN

PREGNANT OR BREASTFEEDING

If pregnant or nursing or if you have a serious medical condition, consult a healthcare professional before using this product.

WARNING

WARNINGS: FOR EXTERNAL COSMETIC USE ONLY. If pregnant or nursing or if you have a serious medical condition, consult a healthcare professional before using this product.

Discontinue use if skin irritation or red skin develops, and consult a Physician. Do not use with any other progesterone or progestins. Do not use if the tamper-evident seal is broken or missing. California Prop 65 Law requires this statement: This product contains progesterone, a chemical known only to the State of California to cause cancer. Cease using this product and seek medical attention if skin irritation or other negative reactions occur.

DOSAGE AND USE

Apply once or twice a day. Massage into wrists, inner arms, thighs, chest, or use as directed by your physician. Each 1/4 tsp is 20 mg of progesterone.

PURPOSE

This is a topical cream that contains bio-identical micronized USP progesterone derived from wild yam, blended with phytoestrogens. When applied topically to the skin, it may help to balance your hormones and provide support for peri menopause and menopause.

INDICATIONS AND USAGE

USES: This is a topical cream that contains bio-identical micronized USP progesterone derived from wild yam, blended with phytoestrogens. When applied topically to the skin, it may help to balance your hormones and also to provide support for perimenopause and menopause.

Apply once or twice a day. Massage into wrists, inner arms, thighs, chest, or apply or use as directed by your physician.

QUESTIONS

Contact support@wiseessentials.com

SAFETY

Report Adverse Events click here https://www.accessdata.fda.gov/scripts/medwatch/

FDA Safety Recalls Click here https://www.fda.gov/safety/recalls-market-withdrawals-safety-alerts

Presence in Breast Milk Click here https://www.ncbi.nlm.nih.gov/books/NBK501345/

DISCLAIMER

Disclaimer: This drug has not been found by FDA to be safe and effective, and this labeling has not been approved by FDA. For further information about unapproved drugs For further information about unapproved drugs, https://www.fda.gov/drugs/enforcement-activities-fda/unapproved-drugs

RELATED RESOURCES

Medline Plus. Click here https://vsearch.nlm.nih.gov/vivisimo/cgi-bin/query-meta?v:project=medlineplus&query=PROGESTERONE&_gl=1*f9papn*_ga*MTc2NTIwMjU3MS4xNzY1Njc2NTE5*_ga_7147EPK006*czE3NjU2NzY1MTgkbzEkZzEkdDE3NjU2NzY4NzEkajI1JGwwJGgw*_ga_P1FPTH9PL4*czE3NjU2NzY1MTgkbzEkZzEkdDE3NjU2NzY4NzEkajI1JGwwJGgw

Clinical Trials.Click here https://www.clinicaltrials.gov/search?term=PROGESTERONE&viewType=Table#classicRedirect

Biochemcical Date Summary. Click here. https://go.drugbank.com/drugs/DB00396

INACTIVE INGREDIENTS

Wild Yam Extract, Dioscorea Villosa, Polyacrylamide/Isoparraffin, Laureth, USP Micronized Progesterone (from Wid Yam), Emulsifying Wax NF, Coco Caprylate Caprate, Radish Root Extract, Glycerin Stearate, Olive M 1000, Chaste Tree Berry Extract, Squalane Oil, Cholesterol, Jojoba Oil, Squalane Oil, Vitamins D, Cholesterol, Extracts of Dong Quai, Black Cohosh